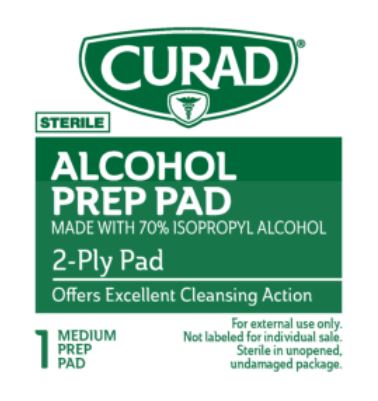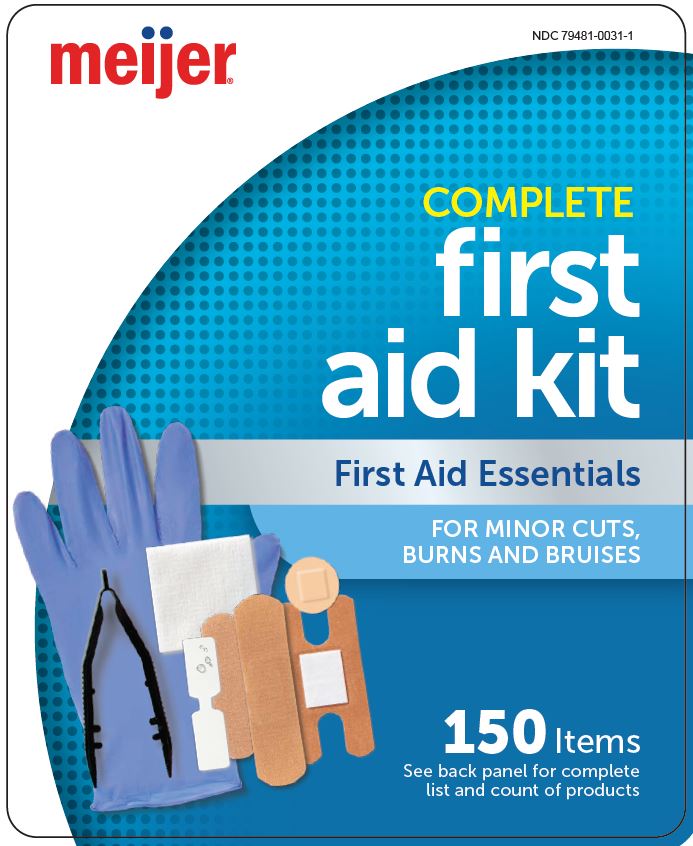 DRUG LABEL: Meijer
NDC: 79481-0031 | Form: KIT | Route: TOPICAL
Manufacturer: Meijer Distribution, Inc.
Category: otc | Type: HUMAN OTC DRUG LABEL
Date: 20250703

ACTIVE INGREDIENTS: ISOPROPYL ALCOHOL 70 mL/100 mL
INACTIVE INGREDIENTS: WATER

79481-0031

Active ingredient

Isoporpyl alcohol 70% v/v

Purpose

Antiseptic

Uses

- for preparation of the skin prior to injection
- first aid antiseptic to help prevent infection in minor cuts, scrapes and burns

Warnings

For external use only. Flammable, keep away from fire or flame.

Do not use

- with electrocautery procedures
- longer than 1 week unless directed by a physician

When using this product

- do not get into eyes
- do not apply over large areas of the body
- in case of deep or puncture wounds, animal bites or serious burns, consult a doctor

Stop use and ask a doctor if

- irritation and redness develop
- condition gets worse or persists for more than 72 hours

Keep out of reach of children.

If accidentally swallowed, seek medical assistance or immediately contact a Poison Control Center.

Directions

- apply to skin as needed
- discard after single use

Inactive ingredient

water

Manufacturing Information

Distributed by:

Meijer Distribution, Inc.

2929 Walker Ave Nw Grand Rapids MI 49544 USA

www.meijer.com

Made in China

V1 RJ22PAN

REF: MJFAK150